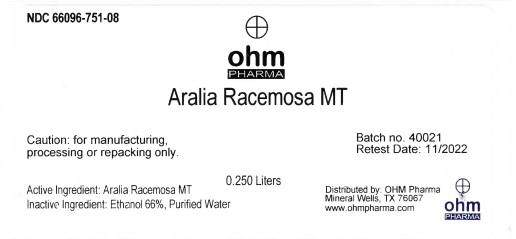 DRUG LABEL: Aralia Racemosa MT
NDC: 66096-751 | Form: LIQUID
Manufacturer: OHM PHARMA INC.
Category: homeopathic | Type: HUMAN PRESCRIPTION DRUG LABEL
Date: 20211228

ACTIVE INGREDIENTS: ARALIA RACEMOSA ROOT 0.25 1/0.25 L
INACTIVE INGREDIENTS: WATER; ALCOHOL

Aralia Racemosa MT

Active Ingredient: Aralia Racemosa MT

INDICATIONS AND USAGE

Batch no. 40021

Restest Date: 11/2022

Caution: for manufacturing,processing or repacking only.

Caution: for manufacturing,
processing or repacking only.

Inactive Ingredient:

Ethanol 66%, Purified Water

QUESTIONS

Distributed by: OHM Pharma

Mineral Wells, TX 76067

www.ohmpharma.com

PACKAGE LABEL

NDC: 66096-751-08

ohm

PHARMA

Aralia Racemosa MT

0.250 Liters

Caution: for manufacturing,

processing or repacking only.

Active Ingredient: Ariala Racemosa MT

Inactive Ingredient: Ethanol 66%, Purified Water

Batch no. 40021

Retest Date: 11/2022

Distributed by: OHM Pharma

Mineral Wells, TX 76067

www.ohmpharma.com